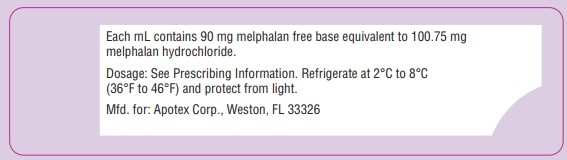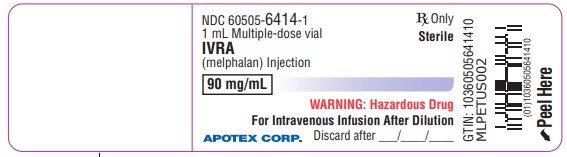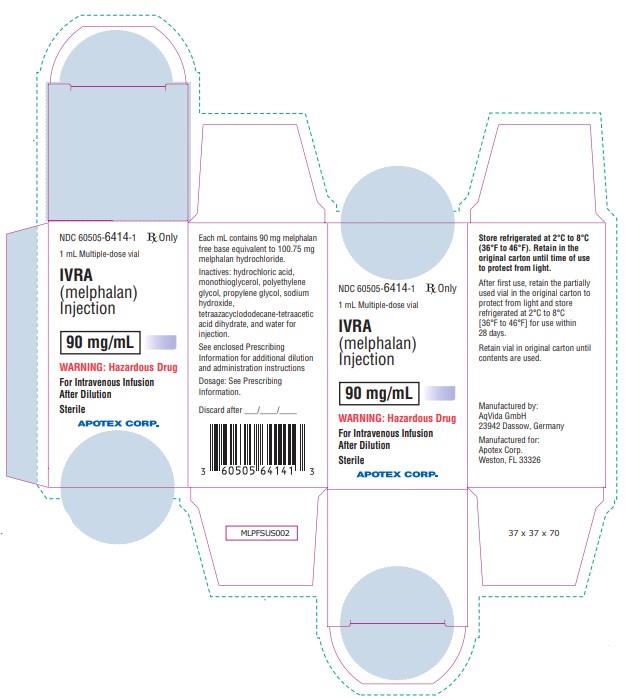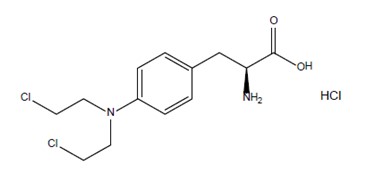 DRUG LABEL: IVRA 
NDC: 60505-6414 | Form: INJECTION, SOLUTION
Manufacturer: Apotex Corp
Category: prescription | Type: HUMAN PRESCRIPTION DRUG LABEL
Date: 20250904

ACTIVE INGREDIENTS: MELPHALAN HYDROCHLORIDE 90 mg/1 mL
INACTIVE INGREDIENTS: PROPYLENE GLYCOL 170 mg/1 mL; MONOTHIOGLYCEROL 5 mg/1 mL; WATER 0.025 mg/1 mL; Tetraxetan 0.5 mg/1 mL; Hydrochloric Acid; Sodium Hydroxide; Sodium Chloride; Polyethylene Glycol 400

HIGHLIGHTS OF PRESCRIBING INFORMATION

These highlights do not include all the information needed to use IVRA safely and effectively. See full prescribing information for IVRA. IVRA (melphalan) injection, for intravenous use Initial U.S. Approval: 1964

WARNING: SEVERE BONE MARROW SUPPRESSION, HYPERSENSITIVITY and LEUKEMOGENICITY

See full prescribing information for complete boxed warning.

- Severe bone marrow suppression with resulting infection or bleeding may occur. Controlled trials comparing intravenous melphalan to oral melphalan have shown more myelosuppression with the intravenous formulation. Monitor hematologic laboratory parameters (5.1).
- Hypersensitivity reactions, including anaphylaxis, have occurred in approximately 2% of patients who received the intravenous formulation of melphalan. Discontinue treatment with IVRA for serious hypersensitivity reactions (5.4).
- Melphalan produces chromosomal aberrations in vitro and in vivo. IVRA should be considered potentially leukemogenic in humans (5.5).

1 INDICATIONS AND USAGE

IVRA is an alkylating drug indicated for palliative treatment of patients with multiple myeloma for whom oral therapy is not appropriate. (1)

2 DOSAGE AND ADMINISTRATION

Recommended dosage is 16 mg/m^2 administered intravenously over 15 to 20 minutes at 2-week intervals for 4 doses, then, after adequate recovery from toxicity, at 4-week intervals. (2.2)

See full prescribing information for preparation and administration instructions. (2.3)

3 DOSAGE FORMS AND STRENGTHS

Injection: 90 mg/mL of melphalan in a multiple-dose vial. (3)

4 CONTRAINDICATIONS

History of severe hypersensitivity to melphalan. (4)

5 WARNINGS AND PRECAUTIONS

- Gastrointestinal toxicity: Nausea, vomiting, diarrhea, or oral mucositis may occur; provide supportive care using antiemetic and antidiarrheal medications as needed. (5.2)
- Embryo-fetal toxicity: Can cause fetal harm. Advise females of reproductive potential and males with female partners of reproductive potential of potential risk to fetus and to use effective contraception. (5.6, 8.1)
- Infertility: Melphalan may cause ovarian function suppression or testicular suppression. (5.7)

6 ADVERSE REACTIONS

Most common adverse reactions (≥50%) are neutrophil count decreased, white blood cell count decreased, lymphocyte count decreased, platelet count decreased, diarrhea, nausea, fatigue, hypokalemia, anemia, and vomiting. (6.1)

To report SUSPECTED ADVERSE REACTIONS, contact Apotex Corp. at 1-800-706-5575 or FDA at 1-800-FDA-1088 or www.fda.gov/medwatch.

8 USE IN SPECIFIC POPULATIONS

Lactation: Advise not to breastfeed. (8.2)

Renal insufficiency (BUN ≥30 mg/dL): Consider dosage reduction (2.2, 8.6)

FULL PRESCRIBING INFORMATION

WARNING: SEVERE BONE MARROW SUPPRESSION, HYPERSENSITIVITY and LEUKEMOGENICITY

- Severe bone marrow suppression with resulting infection or bleeding may occur. Controlled trials comparing intravenous melphalan to oral melphalan have shown more myelosuppression with the intravenous formulation. Monitor hematologic laboratory parameters [see Warnings and Precautions (5.1)].

- Hypersensitivity reactions, including anaphylaxis, have occurred in approximately 2% of patients who received the intravenous formulation of melphalan. Discontinue treatment with IVRA for serious hypersensitivity reactions [see Warnings and Precautions (5.4)].

- Melphalan produces chromosomal aberrations in vitro and in vivo. IVRA should be considered potentially leukemogenic in humans [see Warnings and Precautions (5.5)].

1 INDICATIONS AND USAGE

Multiple Myeloma-Palliative Treatment

IVRA is indicated for the palliative treatment of patients with multiple myeloma for whom oral therapy is not appropriate.

2 DOSAGE AND ADMINISTRATION

2.1 Recommended Dosage

The recommended dosage is 16 mg/m^2 intravenously over 15 to 20 minutes at 2-week intervals for 4 doses, then at 4-week intervals until unacceptable toxicity.

Administer prophylactic antiemetics [see Warnings and Precautions (5.2)].

2.2 Dosage Modifications for Adverse Reactions

See Table 1 for dosage modifications for adverse reactions related to bone marrow suppression [see Warnings and Precautions (5.1)].

Table 1. Dosage Modifications for Adverse Reaction: Bone Marrow Suppression

Parameter |  | Dosing Recommendations
White Blood Cell Count (WBC/mm^3) | Platelet Count (Per mcL) | Dosing Recommendations
Greater than or equal to 4,000 | Greater than or equal to 100,000 | Continue full IVRA dose
Greater than or equal to 3,000 | Greater than or equal to 75,000 | Reduce IVRA to 75% of full dose
Greater than or equal to 2,000 | Greater than or equal to 50,000 | Reduce IVRA to 50% of full dose
Less than 2,000 | Less than 50,000 | Withold IVRA

2.3 Dosage Modifications for Renal Impairment

Consider a dosage reduction of up to 50% in patients with renal insufficiency (BUN ≥30 mg/dL) [see Use in Specific Populations (8.6)].

2.4 Preparation and Administration

Preparation

- IVRA is a hazardous drug. Follow applicable special handling and disposal procedures^1.
- Parenteral drug products should be visually inspected for particulate matter and discoloration prior to administration whenever solution and container permit. If either occurs, do not use this product.
- IVRA is light sensitive. After first use, store the partially used vial refrigerated at 2°C to 8°C [36°F to 46°F] in the original carton for use within 28 days and then discard the remaining contents. Retain vial in original carton until contents are used.
- Do not mix IVRA with other melphalan hydrochloride drug products.

Dilution

- Calculate the required volume of IVRA needed for a patient’s dose and withdraw that volume from the vial(s).
- Add the required volume of IVRA to the appropriate volume of 0.9% Sodium Chloride Injection to obtain a solution with a concentration not greater than 0.45 mg/mL. Immediately mix the contents of infusion vigorously by manual rotation. The diluted product is stable for 1 hour at room temperature.

Administration

- Infuse over 15 to 20 minutes via an injection port or central venous catheter. Complete administration within 60 minutes of dilution.
- IVRA may cause local tissue damage should extravasation occur. Administer IVRA only by injecting slowly into a fast-running intravenous infusion via an injection port or, central venous access line.

3 DOSAGE FORMS AND STRENGTHS

Injection: 90 mg/mL melphalan as a clear colorless to yellow solution in a multiple-dose vial for dilution.

4 CONTRAINDICATIONS

IVRA is contraindicated in patients with a history of severe hypersensitivity to melphalan. Reactions have included anaphylaxis [see Warnings and Precautions (5.4)].

5 WARNINGS AND PRECAUTIONS

5.1 Bone Marrow Suppression

IVRA causes bone marrow suppression in most patients.

Obtain complete blood counts with differential at the start of therapy and prior to each subsequent dose of IVRA. Withhold treatment for grade 3 thrombocytopenia and/ or leukopenia until blood counts have returned to grade 2 [see Dosage and Administration (2.2)]. Consider dose adjustment on the basis of blood counts at the nadir and day of treatment.

5.2 Gastrointestinal Toxicity

Gastrointestinal disturbances such as nausea and vomiting, diarrhea, and oral ulceration can occur with melphalan treatment.

Severe mucositis, stomatitis, colitis, diarrhea, and hemorrhage of the gastrointestinal tract occur at high doses (greater than 100 mg/m^2 6 times the recommended approved dose).

Use prophylactic antiemetics [see Dosage and Administration (2.1)]. Provide supportive care for nausea, vomiting, diarrhea, and mucositis.

5.3 Hepatotoxicity

Hepatic disorders ranging from abnormal liver function tests to clinical manifestations such as hepatitis and jaundice have been reported during treatment with melphalan. Hepatic veno-occlusive disease has been reported. Monitor liver enzymes as clinically indicated.

5.4 Hypersensitivity

Acute hypersensitivity reactions including anaphylaxis were reported in 2.4% of 425 patients receiving melphalan injection for myeloma. These reactions were characterized by urticaria, pruritus, edema, skin rashes, and in some patients, tachycardia, bronchospasm, dyspnea, and hypotension. These patients appeared to respond to antihistamine and corticosteroid therapy. If a hypersensitivity reaction occurs, intravenous or oral melphalan should not be readministered since hypersensitivity reactions have also been reported with oral melphalan. Cardiac arrest has also been reported in association with such reports.

Discontinue treatment with IVRA for serious hypersensitivity reactions.

5.5 Secondary Malignancies

Melphalan has been shown to cause chromatid or chromosome damage in humans. Secondary malignancies, including acute nonlymphocytic leukemia, myeloproliferative syndrome, and carcinoma, have been reported in patients with cancer treated with alkylating agents (including melphalan). Some patients also received other chemotherapeutic agents or radiation therapy. The potential benefits from melphalan therapy must be weighed on an individual basis against the possible risk of the induction of a second malignancy.

5.6 Embryo-Fetal Toxicity

Based on its mechanism of action, IVRA can cause fetal harm when administered to a pregnant woman. Melphalan is genotoxic, targets actively dividing cells, and was embryolethal and teratogenic in rats. While adequate animal studies have not been conducted with intravenous melphalan, oral (6 to 18 mg/m^2/day for 10 days) and IP (18 mg/m^2) administration in rats was embryolethal and teratogenic. Malformations resulting from melphalan included alterations of the brain (underdevelopment, deformation, meningocele, and encephalocele) and eye (anophthalmia and microphthalmos), reduction of the mandible and tail, as well as hepatocele (exomphaly).

If this drug is used during pregnancy or if the patient becomes pregnant while taking this drug, advise a pregnant woman of the of potential risk to the fetus. Advise females of reproductive potential to use effective contraception during treatment with IVRA and for 6 months after the last dose. Advise males with female partners of reproductive potential to use effective contraception during treatment with IVRA and for 3 months after the last dose [see Use in Specific Populations (8.1, 8.3)].

5.7 Infertility

Melphalan causes suppression of ovarian function in premenopausal women, resulting in amenorrhea in a significant number of patients. Reversible and irreversible testicular suppression have also been reported [see Use in Specific Populations (8.3)].

6 ADVERSE REACTIONS

The following clinically significant adverse reactions are described elsewhere in the labeling:

- Bone Marrow Suppression [see Warnings and Precautions (5.1)]
- Gastrointestinal Toxicity [see Warnings and Precautions (5.2)]
- Hepatotoxicity [see Warnings and Precautions (5.3)]
- Hypersensitivity [see Warnings and Precautions (5.4)]
- Secondary Malignancies [see Warnings and Precautions (5.5)]

6.1 Clinical Trials Experience

Because clinical studies are conducted under widely varying conditions, adverse reaction rates observed in the clinical studies of melphalan may not reflect the rates observed in practice.

The most common adverse reactions observed in at least 50% of patients with multiple myeloma treated with melphalan were neutrophil count decreased, white blood cell count decreased, lymphocyte count decreased, platelet count decreased, diarrhea, nausea, fatigue, hypokalemia, anemia, and vomiting.

Palliative Treatment of Patients with Multiple Myeloma

The safety of melphalan was evaluated in 295 patients with multiple myeloma in the randomized clinical trial [see Clinical Studies (14)]. One hundred and ninety-five patients were administered intravenous melphalan at a dosage of 16 mg/m^2

q 2 weeks x 4 (over 6 weeks) followed by the same dose every 4 weeks. One hundred patients were administered oral melphalan at a dosage of 0.15 mg/kg/day x 7 followed by 0.05 mg/kg/day when WBC counts began to rise.

Severe myelotoxicity (WBC ≤1,000 and/or platelets ≤25,000) was more common in the intravenous melphalan arm (28%) than in the oral melphalan arm (11%).

7 DRUG INTERACTIONS

7.1 Effect of Other Drugs on IVRA

Cisplatin

Concomitant use with cisplatin may alter melphalan clearance by inducing renal dysfunction. Consider intravenous IVRA dosage reduction in patients with renal insufficiency following concomitant use with cisplatin [see Dosage and Administration (2.2)].

7.2 Effect of IVRA on Other Drugs

BCNU

Concomitant use with BCNU may reduce the threshold for lung toxicity. Monitor for increased lung toxicity.

7.3 Cyclosporine

Concomitant use with cyclosporine may increase the risk of developing severe renal failure [see Clinical Pharmacology (12.3)]. Consider intravenous IVRA dosage reduction in patients with renal insufficiency following concomitant use with cyclosporine [see Dosage and Administration (2.2)].

8 USE IN SPECIFIC POPULATIONS

8.1 Pregnancy

Risk Summary

Based on its mechanism of action and findings from animal studies, IVRA can cause fetal harm when administered to a pregnant woman. There are no available data on IVRA use in pregnant women to evaluate for a drug-associated risk. In rats, melphalan was embryolethal and teratogenic at doses lower than the highest recommended clinical dose (see Data). If this drug is used during pregnancy, or if the patient becomes pregnant while taking this drug, the patient should be apprised of the potential risk to the fetus.

The background risk in the U.S. general population of major birth defects is 2 to 4% and of miscarriage is 15 to 20% of clinically recognized pregnancies.

Data

Animal Data

Adequate animal studies have not been conducted with intravenous melphalan. Melphalan was embryolethal and teratogenic in rats following oral administration of 6 to 18 mg/m^2/day for 10 days (0.06 to 0.18 times the highest recommended clinical dose of 100 mg/m^2/day) and intraperitoneal administration of 18 mg/m^2 (0.18 times the highest recommended clinical dose). Malformations resulting from melphalan administration included alterations of the brain (underdevelopment, deformation, meningocele, and encephalocele) and eye (anophthalmia and microphthalmos), reduction of the mandible and tail, and hepatocele (exomphaly).

8.2 Lactation

Risk Summary

There are no data on the presence of melphalan in human milk, the effects on the breastfed child, or the effects on milk production. Because of the potential for serious adverse reactions in a breastfed child, advise women not to breastfeed during treatment with IVRA and for 1 week following the last dose.

8.3 Females and Males of Reproductive Potential

IVRA can cause fetal harm when administered to a pregnant woman [see Use in Specific Populations (8.1)].

Contraception

Females

Advise females of reproductive potential to use effective contraception during treatment with IVRA and for 6 months after the last dose.

Males

Melphalan may damage spermatozoa and testicular tissue, resulting in possible genetic fetal abnormalities. Advise males with female partners of reproductive potential to use effective contraception during treatment with IVRA and for 3 months after the last dose [see Nonclinical Toxicology (13.1)].

Infertility

Females

Melphalan causes suppression of ovarian function in premenopausal women, resulting in amenorrhea in a significant number of patients.

Males

Reversible and irreversible testicular suppression has been reported in male patients after administration of melphalan.

8.4 Pediatric Use

The safety and effectiveness of IVRA in pediatric patients have not been established.

8.5 Geriatric Use

Clinical studies of melphalan did not include sufficient numbers of subjects aged 65 and over to determine whether they respond differently from younger subjects. Other reported clinical experience has not identified differences in responses between the elderly and younger patients. In general, dose selection for an elderly patient should be cautious, usually starting at the low end of the dosing range, reflecting the greater frequency of decreased hepatic, renal, or cardiac function, and of concomitant disease or other drug therapy.

8.6 Renal Impairment

Consider a dosage reduction in patients with renal insufficiency receiving intravenous IVRA [see Dosage and Administration (2.2)]. In one trial, increased bone marrow suppression was observed in patients with elevated BUN [see Clinical Pharmacology (12.3)].

10 OVERDOSAGE

Overdoses resulting in death have been reported. Overdoses, including doses up to 290 mg/m^2 (18 times the recommended dose), have produced the following symptoms: severe nausea and vomiting, decreased consciousness, convulsions, muscular paralysis, and cholinomimetic effects. Severe mucositis, stomatitis, colitis, diarrhea, and hemorrhage of the gastrointestinal tract occur at high doses (greater than 100 mg/m^2 6 times the recommended dose). Elevations in liver enzymes and veno-occlusive disease have occurred. Significant hyponatremia caused by an associated inappropriate secretion of ADH syndrome has been observed. Nephrotoxicity and adult respiratory distress syndrome have been reported.

The principal toxic effect is bone marrow suppression. In the event of an overdosage, monitor hematologic parameters for 3 to 6 weeks. General supportive measures together with appropriate blood transfusions and antibiotics should be instituted as deemed necessary by the physician. This drug is not removed from plasma to any significant degree by hemodialysis or hemoperfusion.

11 DESCRIPTION

IVRA contains melphalan which is an alkylating drug. The chemical name of melphalan hydrochloride is 4-[bis(2-chloroethyl)amino]-L-phenylalanine hydrochloride. The molecular formula is C13H18Cl2N2O2 • HCl and the molecular weight is 341.67. The structural formula is:

Melphalan hydrochloride is a white to off-white powder, with a melting range of 199°C to 201°C. It is practically insoluble in water, but freely soluble in 1N HCl and methanol.

IVRA is supplied as a sterile, clear colorless to yellow solution in a multiple-dose vial for intravenous use. Each mL contains 90 mg melphalan free base equivalent to 100.75 mg melphalan hydrochloride, 170 mg propylene glycol, 5 mg monothioglycerol, 0.5 mg (1,4,7,10-tetraazacyclododecane-1,4,7,10-tetraacetic acid dihydrate), and 0.025 mL water for injection in polyethylene glycol 400. May contain hydrochloric acid and/or sodium hydroxide for pH adjustment. The pH of the drug product solution after dilution with 0.9% sodium chloride ranges from 2.4 - 3.5. Each mL contains 90 mg melphalan free base equivalent to 100.75 mg melphalan hydrochloride.

12 CLINICAL PHARMACOLOGY

12.1 Mechanism of Action

Melphalan is an alkylating agent of the bischloroethylamine type. As a result, its cytotoxicity appears to be related to the extent of its interstrand cross-linking with DNA, probably by binding at the N^7 position of guanine. Like other bifunctional alkylating agents, it is active against both resting and rapidly dividing tumor cells.

12.2 Pharmacodynamics

Due to lack of information, melphalan exposure-response relationships and the time course of pharmacodynamic response are unknown.

12.3 Pharmacokinetics

The mean ±SD melphalan peak plasma concentration is 1.2 ± 0.4 following an intravenous dosage of 10 mg/m^2 (0.62 times the approved recommended dosage) and 2.8 ± 1.9 mcg/mL following an intravenous dosage of 20 mg/m^2 (1.25 times the approved recommended dosage) in myeloma patients.

Distribution

The melphalan steady-state volume of distribution is 0.5 L/kg. Melphalan penetration into cerebrospinal fluid (CSF) is low.

The mean melphalan plasma protein binding ranges from 53% to 92% with approximately 30% irreversible (covalent). Serum albumin accounts for approximately 40% to 60% and α1-acid glycoprotein approximately 20% of the plasma protein binding.

Elimination

The melphalan elimination half-life is approximately 75 minutes. Mean total body melphalan clearance varied among studies, but typical values of approximately 7 to 9 mL/min/kg (250 to 325 mL/min/m^2) were observed.

Metabolism

Melphalan primarily metabolized by hydrolysis to monohydroxymelphalan and dihydroxymelphalan, which are inactive.

Excretion

Following a radiolabeled dose of intravenous melphalan in 9 patients with cancer, the mean (± SD) excretion of melphalan over 24 hours was 13% ± 5.4% of the total dose.

Specific Populations

Patients with renal Impairment

Although melphalan renal clearance appears to be low, one study reported an increase in the occurrence of severe leukopenia in patients with BUN levels ≥30 mg/dL after 10 weeks of therapy. A 50% reduction in the IV melphalan dosage decreased the incidence of severe bone marrow suppression in the latter portion of this study.

Drug Interaction Studies

Cyclosporine

Patients treated with a single dose of intravenous melphalan followed by standard oral doses of cyclosporine were reported to develop severe renal failure.

Immunoglobulins

Interactions between melphalan and immunoglobulins are negligible.

13 NONCLINICAL TOXICOLOGY

13.1 Carcinogenesis, Mutagenesis, Impairment of Fertility

Adequate and well-controlled carcinogenicity studies with melphalan have not been conducted in animals. However, intraperitoneal (IP) administration of melphalan in rats (5.4 to 10.8 mg/m^2) and in mice (2.25 to 4.5 mg/m^2) 3 times per week for 6 months followed by 12 months post-dose observation produced peritoneal sarcoma and lung tumors, respectively.

Intramuscular administration of melphalan at 6 and 60 mg/m^2 produced structural aberrations of the chromatid and chromosomes in bone marrow cells of Wistar rats.

14 CLINICAL STUDIES

Palliative Treatment of Patients with Multiple Myeloma

A randomized trial compared prednisone plus intravenous melphalan to prednisone plus oral melphalan in the treatment of myeloma. Both arms received oral prednisone starting at 0.8 mg/kg/day with doses tapered over 6 weeks. Melphalan doses in each arm were: Arm 1: Oral melphalan 0.15 mg/kg/day x 7 followed by 0.05 mg/kg/day when WBC began to rise. Arm 2: Intravenous melphalan 16 mg/m^2 q 2 weeks x 4 (over 6 weeks) followed by the same dose every 4 weeks.

One hundred seven patients were randomized to the oral melphalan arm and 203 patients to the intravenous melphalan arm. More patients had a poor-risk classification (58% versus 44%) and high tumor load (51% versus 34%) on the oral compared to the intravenous arm (P<0.04). Response rates at week 22 are shown in the following table:

Table 2. Response Rates at Week 22 In Patients with Multiple Myeloma Who Received Oral or Intravenous Melphalan with Prednisone

Initial Arm | Evaluable Patients | Responders n (%) | P
Oral melphalan | 100 | 44 (44%) | P>0.2
Intravenous melphalan | 195 | 74 (38%) | P>0.2

Because of changes in protocol design after week 22, other efficacy parameters such as response duration and survival cannot be compared.

15 REFERENCES

1. OSHA Hazardous Drugs https://www.osha.gov/hazardous-drugs

16 HOW SUPPLIED/STORAGE AND HANDLING

How Supplied

IVRA (melphalan) injection is a clear colorless to yellow solution supplied in a carton containing one 90 mg/mL amber glass multiple-dose vial for dilution. (NDC 60505-6414-1).

Storage and Handling

Store IVRA refrigerated at 2°C to 8°C (36°F to 46°F). IVRA is light sensitive. Retain in original carton when not in use.

IVRA is a hazardous drug^1. Follow special handling and disposal procedures^1.

17 PATIENT COUNSELING INFORMATION

Low Blood Cell Counts

Advise patients to report any signs or symptoms of thrombocytopenia, leukopenia (neutropenia and lymphopenia), and anemia. Inform patients of the need for routine blood counts [see Warnings and Precautions (5.1)].

Mucositis

Inform patients of the signs and symptoms of mucositis. Instruct patients on ways to reduce the risk of its development, and on ways to maintain nutrition and control discomfort if it occurs [see Warnings and Precautions (5.2)].

Allergic Reactions

Advise patients to immediately report symptoms of hypersensitivity reactions including changes involving the skin, breathing or heart rate, so that antihistamine or corticosteroid therapy can be administered [see Warnings and Precautions (5.4)].

Secondary Malignancies

Advise patients of the potential long-term risks related to secondary malignancy [see Warnings and Precautions (5.5)].

Embryo Fetal Toxicity

- Advise pregnant women of the potential risk to a fetus [see Warnings and Precautions (5.6) and Use in Specific Populations (8.1)].
- Advise females of reproductive potential to use effective contraception during and for 6 months after treatment with IVRA. Advise males with female partners of reproductive potential to use effective contraception during treatment with IVRA and for 3 months after the last dose. Advise females to contact their healthcare provider if they become pregnant, or if pregnancy is suspected, while taking IVRA [see Warnings and Precautions (5.6) and Use in Specific Populations (8.1)].
- Inform females of reproductive potential about the risk for infertility. Advise males that reversible and irreversible testicular suppression have been reported [see Warnings and Precautions (5.7)].
- Advise women not to breastfeed during treatment with IVRA and for 1 week following the last dose [see Use in Specific Populations (8.2)].

Manufactured by:

AqVida GmbH

23942 Dassow Germany

Manufactured for:

Apotex Corp.

Weston, Florida, USA 33326

Rev 1

PRINCIPAL DISPLAY PANEL

IVRA (melphalan) Injection

90 mg/mL- Bottle label

Multiple-Dose Vial

NDC# 60505-6414-1

PRINCIPAL DISPLAY PANEL

IVRA (melphalan) Injection

90 mg/mL - Bottle Carton

Multiple-Dose Vial

NDC# 60505-6414-1